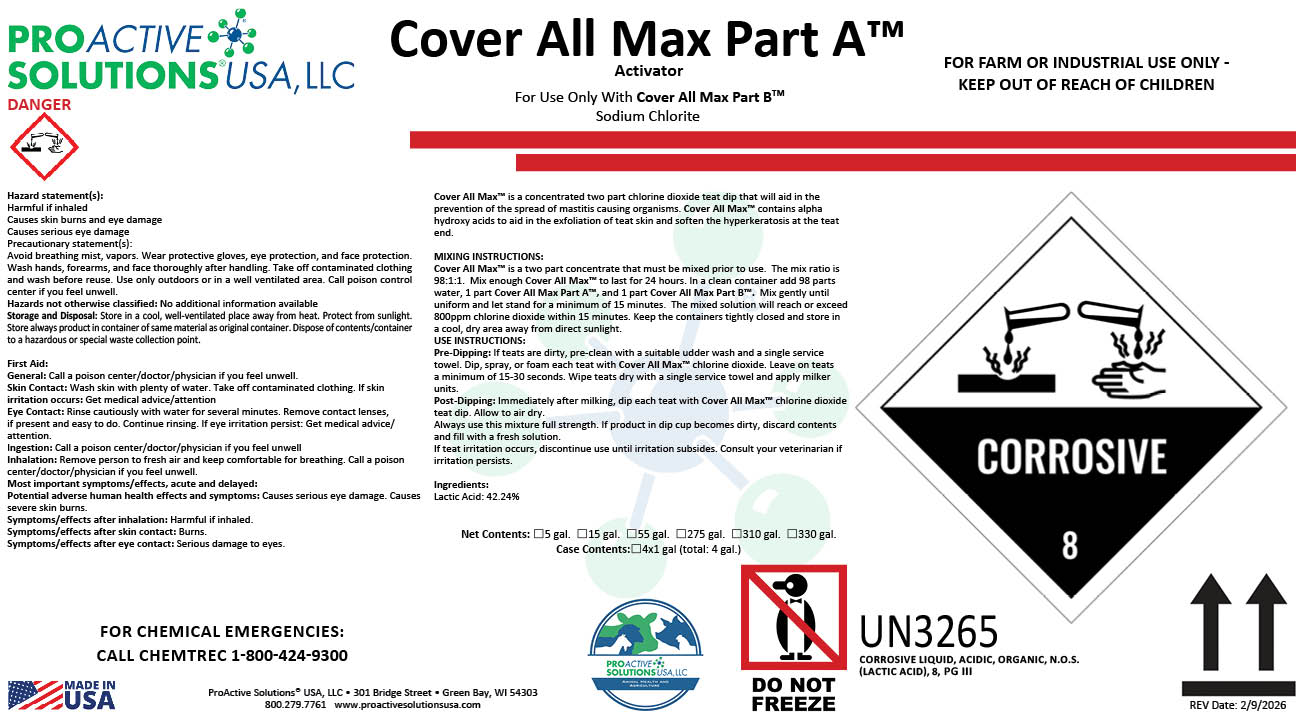 DRUG LABEL: Cover All Max Part A
NDC: 63927-4131 | Form: SOLUTION
Manufacturer: Proactive Solutions USA, LLC
Category: animal | Type: OTC ANIMAL DRUG LABEL
Date: 20260210

ACTIVE INGREDIENTS: LACTIC ACID 42.24 kg/100 kg

Cover All Max Part A

Cover All Max Part A

Cover All Max™ is a concentrated two part chlorine dioxide teat dip that will aid in the
prevention of the spread of mastitis causing organisms. Cover All Max™ contains alpha
hydroxy acids to aid in the exfoliation of teat skin and soften the hyperkeratosis at the teat
end.
MIXING INSTRUCTIONS:
Cover All Max™ is a two part concentrate that must be mixed prior to use. The mix ratio is
98:1:1. Mix enough Cover All Max™ to last for 24 hours. In a clean container add 98 parts
water, 1 part Cover All Max Part A™, and 1 part Cover All Max Part B™. Mix gently until
uniform and let stand for a minimum of 15 minutes. The mixed solution will reach or exceed
800ppm chlorine dioxide within 15 minutes. Keep the containers tightly closed and store in
a cool, dry area away from direct sunlight.
USE INSTRUCTIONS:
Pre-Dipping: If teats are dirty, pre-clean with a suitable udder wash and a single service
towel. Dip, spray, or foam each teat with Cover All Max™ chlorine dioxide. Leave on teats
a minimum of 15-30 seconds. Wipe teats dry with a single service towel and apply milker
units.
Post-Dipping: Immediately after milking, dip each teat with Cover All Max™ chlorine dioxide
teat dip. Allow to air dry.
Always use this mixture full strength. If product in dip cup becomes dirty, discard contents
and fill with a fresh solution.
If teat irritation occurs, discontinue use until irritation subsides. Consult your veterinarian if
irritation persists.
Ingredients:
Lactic Acid: 42.24%

Hazard statement(s):
Harmful if inhaled
Causes skin burns and eye damage
Causes serious eye damage
Precautionary statement(s):
Avoid breathing mist, vapors. Wear protective gloves, eye protection, and face protection.
Wash hands, forearms, and face thoroughly after handling. Take off contaminated clothing
and wash before reuse. Use only outdoors or in a well ventilated area. Call poison control
center if you feel unwell.
Hazards not otherwise classified: No additional information available
Storage and Disposal: Store in a cool, well-ventilated place away from heat. Protect from sunlight.
Store always product in container of same material as original container. Dispose of contents/container
to a hazardous or special waste collection point.
First Aid:
General: Call a poison center/doctor/physician if you feel unwell.
Skin Contact: Wash skin with plenty of water. Take off contaminated clothing. If skin
irritation occurs: Get medical advice/attention
Eye Contact: Rinse cautiously with water for several minutes. Remove contact lenses,
if present and easy to do. Continue rinsing. If eye irritation persist: Get medical advice/
attention.
Ingestion: Call a poison center/doctor/physician if you feel unwell
Inhalation: Remove person to fresh air and keep comfortable for breathing. Call a poison
center/doctor/physician if you feel unwell.
Most important symptoms/effects, acute and delayed:
Potential adverse human health effects and symptoms: Causes serious eye damage. Causes
severe skin burns.
Symptoms/effects after inhalation: Harmful if inhaled.
Symptoms/effects after skin contact: Burns.
Symptoms/effects after eye contact: Serious damage to eyes.